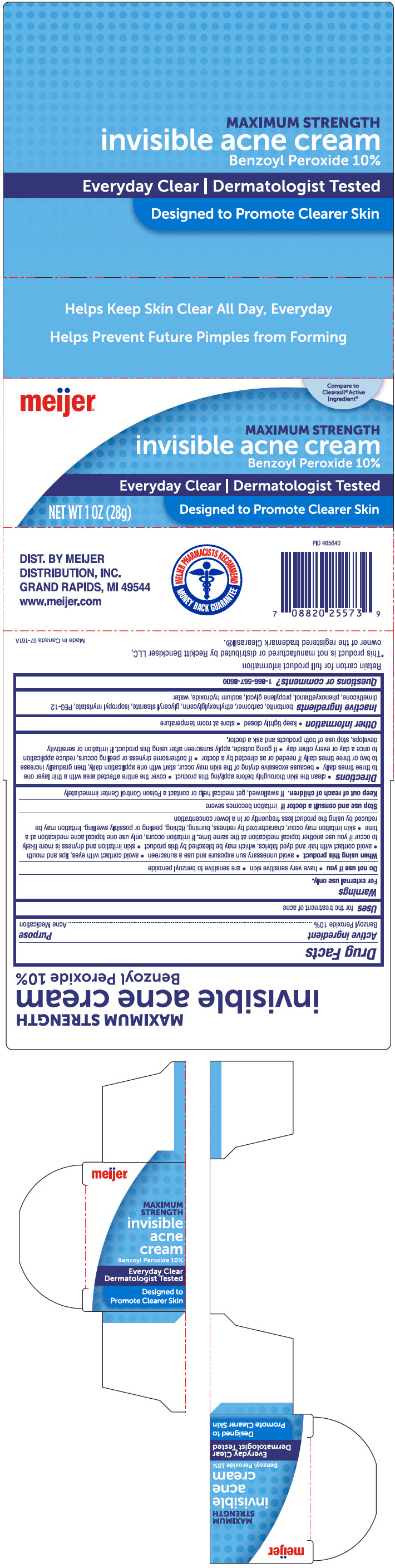 DRUG LABEL: Meijer Invisible Acne
NDC: 41250-348 | Form: CREAM
Manufacturer: Meijer Distribution, Inc
Category: otc | Type: HUMAN OTC DRUG LABEL
Date: 20241106

ACTIVE INGREDIENTS: Benzoyl Peroxide 100 mg/1 g
INACTIVE INGREDIENTS: Bentonite; CARBOMER HOMOPOLYMER, UNSPECIFIED TYPE; Ethylhexylglycerin; GLYCERYL MONOSTEARATE; Isopropyl Myristate; PEG-12 DIMETHICONE (300 CST); Phenoxyethanol; Propylene Glycol; Sodium Hydroxide; Water

Meijer® Invisible Acne Cream
Acne medication

Drug Facts

Active ingredient

Benzoyl Peroxide 10%

Purpose

Acne Medication

Uses

for the treatment of acne

Warnings

For external use only.

Do not use if you

- have very sensitive skin
- are sensitive to benzoyl peroxide

When using this product

- avoid unnecessary sun exposure and use a sunscreen
- avoid contact with eyes, lips and mouth
- avoid contact with hair or dyed fabrics, which may be bleached by this product
- skin irritation and dryness is more likely to occur if you use another topical medication at the same time. If irritation occurs, only use one topical acne medication at a time
- skin irritation may occur, characterized by redness, burning, itching, peeling, or possibly swelling. Irritation may be reduced by using the product less frequently or in a lower concentration

Stop use and ask a doctor if irritation becomes severe

Keep out of reach of children. If swallowed, get medical help or contact a Poison Control Center immediately

Directions

- clean the skin thoroughly before applying this product
- cover the entire affected area with a thin layer one to three times daily
- because excessive drying of the skin may occur, start with one application daily, then gradually increase to two or three times daily if needed or as directed by a doctor
- if bothersome dryness or peeling occurs, reduce application to once a day or every other day
- if going outside, apply sunscreen after using this product. If irritation or sensitivity develops, stop use of both products and ask a doctor.

Other information

- keep tightly closed
- store at room temperature

Inactive ingredients

bentonite, carbomer, ethylhexylglycerin, glyceryl stearate, isopropyl myristate, PEG-12 dimethicone, phenoxyethanol, propylene glycol, sodium hydroxide, water

Questions or comments?

1-866-567-8600

DIST. BY MEIJER
DISTRIBUTION, INC.
GRAND RAPIDS, MI 49544

PRINCIPAL DISPLAY PANEL - 28 g Tube Carton

Compare to
Clearasil® Active
Ingredient*

meijer®

MAXIMUM STRENGTH
invisible acne cream
Benzoyl Peroxide 10%

Everyday Clear | Dermatologist Tested

NET WT 1 OZ (28g)

Designed to Promote Clearer Skin